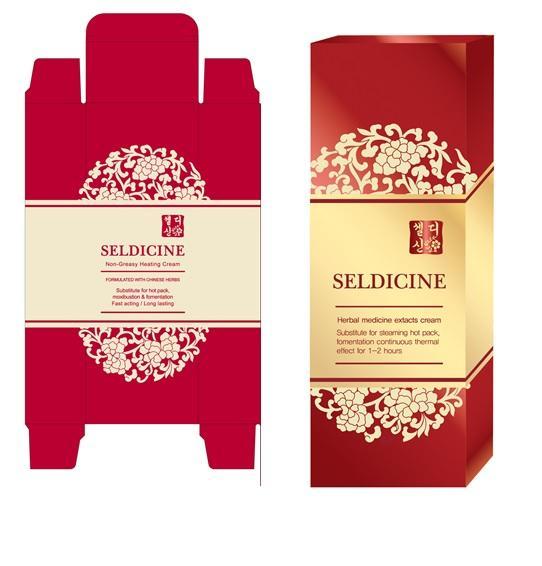 DRUG LABEL: Seldicine (Massage Cream)
NDC: 69083-101 | Form: CREAM
Manufacturer: Orye Life Science Co., Ltd.
Category: otc | Type: HUMAN OTC DRUG LABEL
Date: 20200116

ACTIVE INGREDIENTS: CAMPHOR OIL 1 g/100 g; MENTHOL 1 g/100 g
INACTIVE INGREDIENTS: GLYCERIN; PROPYLENE GLYCOL; CARBOMER COPOLYMER TYPE A; POLYSORBATE 80; METHYLPARABEN; PHENOXYETHANOL; PROPYLPARABEN; CURCUMA LONGA WHOLE; CAPSICUM ANNUUM WHOLE; ARTEMISIA VULGARIS WHOLE; LEDUM PALUSTRE TWIG; ANGELICA GIGAS ROOT OIL; CNIDIUM OFFICINALE ROOT OIL; SOPHORA FLAVESCENS ROOT; GLYCYRRHIZA GLABRA; GARDENIA JASMINOIDES WHOLE; SALVIA MILTIORRHIZA ROOT; WATER; STEARIC ACID

Seldicine (Massage Cream)

Active Ingredients

Camphor 1%
Menthol 1%

Purpose

Topical Analgesic

Uses

For the temporary relief of minor aches and pains of muscles and joints

Warnings

Do not use if you have red rash, swell, itch or any other abnormal physical symptoms while applying it on your body parts
Do not use on injured body parts, eczema or dermatitis
Keep it at a room temperature and out of children’s reach
Be careful not to get in your eyes

Dossage

Apply on body parts, for arms or legs, apply on both sides together and you have better thermo-therapeutical effect

Inactive Ingredients

Ledum Palustre Extract, Angelica Gigas Extract, Cnidium Officinale Root Extract, Sophora Augustifolia Root Extract, Glycyrrhiza Glabra Root Extract, Gradenia Florida Fruit Extract, Salvia Mittiorrhiza Flower Root Extract, Water, Steric Acid, Glycerin, Propylene Glycol, Carbomer, Polysorbate 80, Methylparaben, Phenoxyethanol, Propylparaben, Curcuma Louga Root Extract, Capsicum Annuum Fruit Extract, Artemisia Vulgaris Extract.